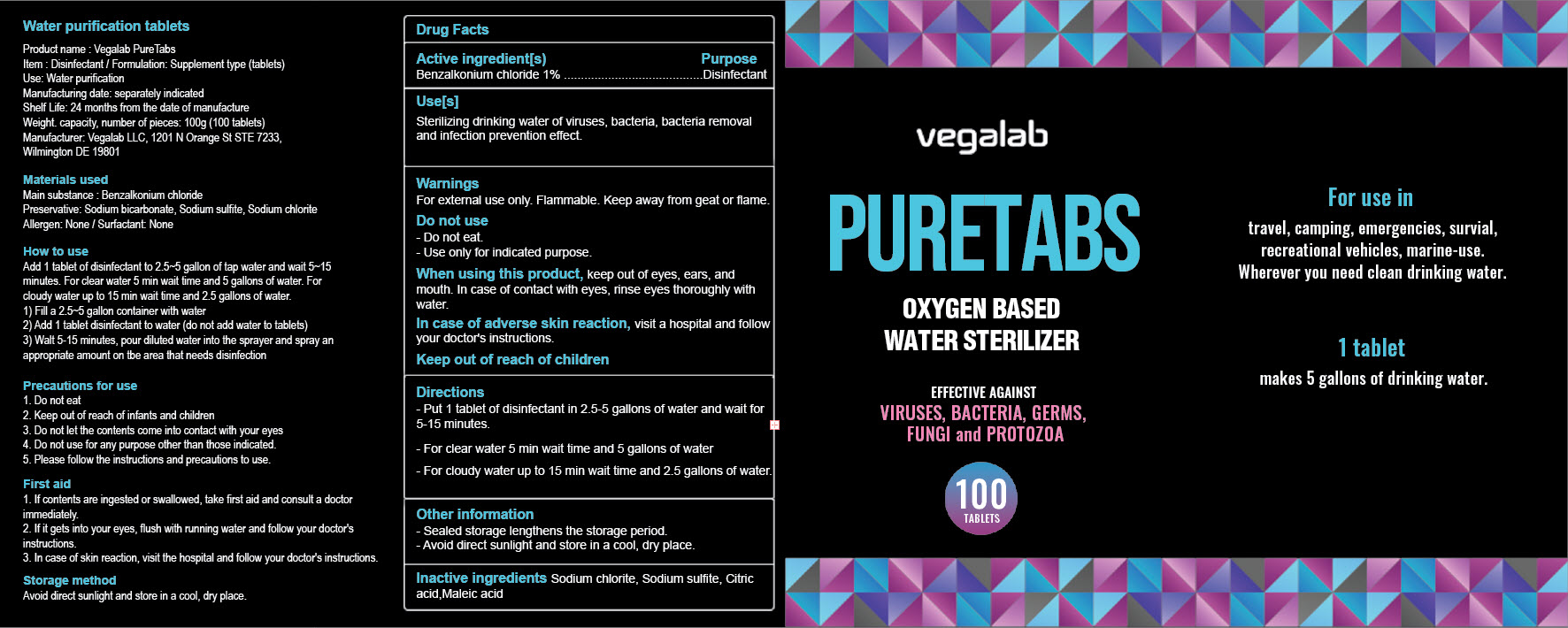 DRUG LABEL: Vegalab PURETABS
NDC: 85289-102 | Form: TABLET, SOLUBLE
Manufacturer: Vegalab LLC
Category: otc | Type: HUMAN OTC DRUG LABEL
Date: 20250304

ACTIVE INGREDIENTS: BENZALKONIUM CHLORIDE 1 g/100 g
INACTIVE INGREDIENTS: SODIUM CHLORITE; MALEIC ACID; SODIUM SULFITE; CITRIC ACID MONOHYDRATE

Active Ingredients:

Benzalkonium Chloride 1%

Purpose:

Disinfectant

Warnings:

For external use only. Flammable. Keep away from geat or flame.

Do Not Use Section:

- Do not eat.

- Use only for indicated purpose

When Using this product:

Keep out of eyes, ears, and mouth. In case of contact with eyes, rinse eyes thoroughly with water.

Use(s):

Sterilizing drinking water of viruses, bacteria, bacteria removal and infection prevention effect.

Directions:

- Put 1 tablet of disinfectant in 2.5-5 gallons of water and wait for 5-15 minutes.

- For clear water 5 min wait time and 5 gallons of water.

- For cloudy water up to 15 min wait time and 2.5 gallons of water.

Ask Doctor:

In case of adverse skin reaction, visit a hospital and follow your doctor's instructions.

Keep out of reach of Children:

Other Information:

- Sealed storage lengthnes the storge period

- Avoid direct sunlight and store in a cool, dry place.

Inactive Ingredient(s):

Sodium chlorite, Sodium sulfite, Citric acid, Maleic acid

Storage:

Avoid direct sunlight and store in a cool, dry place

Precautions:

1. Don not eat.

2. Keep out of reach of infants and children

3. Do not let the contents come into contact with your eyes.

4. Do not use for any purpose other than those indicated.

5. Please follow the instructions and precautions to use.

First Aid:

1. If contents are ingested or swallowed, take first aid and consult a doctor immediately.

2. If it gets into your eyes, flush with running water and follow your doctor's instructions.

3. In case of skin reaction, visit the hospital and follow your doctor's instructions.

Dosage:

Add 1 tablet of disinfectant to 2.5-5 gallon of tap water and wait 5-15 minutes. For clear water 5 min wait time and 5 gallons of water. For cloudy water up to 15 min wait time and 2.5 gallons of water.

1) Fill a 2.5-5 gallon container with water

2) Add 1 tablet disinfectant to water (do not add water to tablets)

3) Wait 5-15 minutes, pour diluted water into the sprayer and spray an apporpriate amount on the area that needs disinfection.